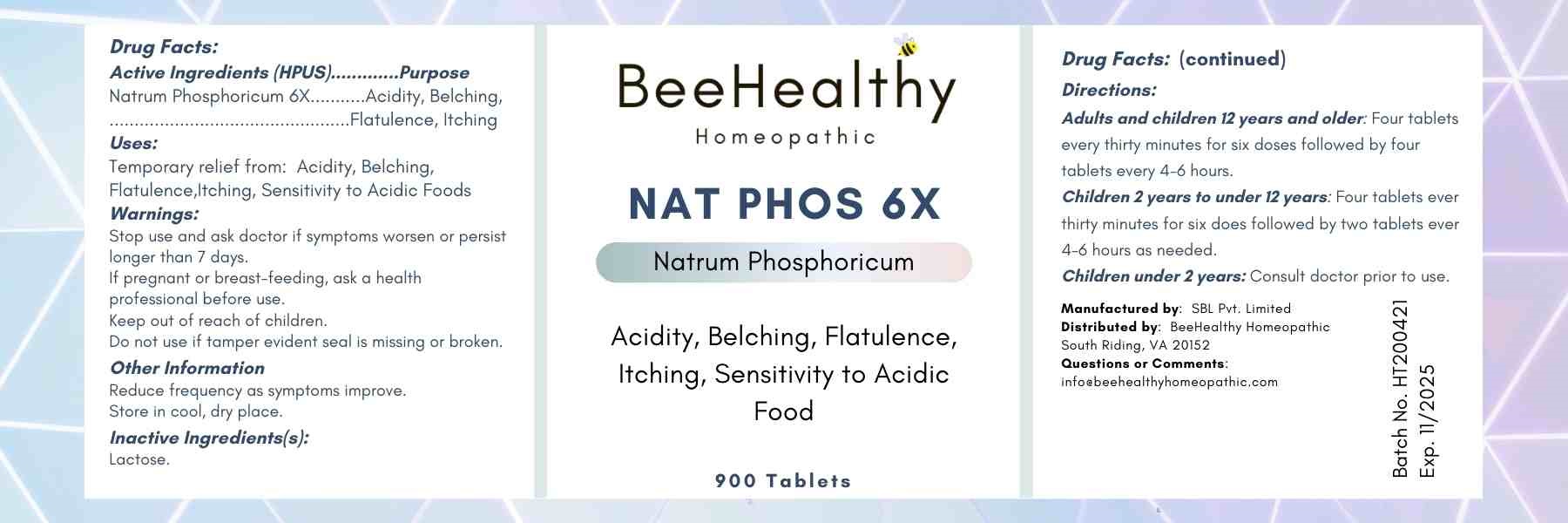 DRUG LABEL: Nat Phos 6X
NDC: 79718-0047 | Form: TABLET
Manufacturer: Warsan Homeopathic
Category: homeopathic | Type: HUMAN OTC DRUG LABEL
Date: 20201211

ACTIVE INGREDIENTS: SODIUM PHOSPHATE DIBASIC DIHYDRATE 6 [hp_X]/1 1
INACTIVE INGREDIENTS: LACTOSE MONOHYDRATE

ACTIVE INGREDIENT

nat phos 6x

INACTIVE INGREDIENT

Lactose

Stop use and ask doctor if symptoms worsen or persist longer than 7 days.

Do not use if tamper evident seal is missing or broken.

INDICATIONS AND USAGE

Temporary relief from acidity, flatulence, belching, itching

PURPOSE

Temporary relief from acidity, flatulence, belching, itching

DOSAGE AND ADMINISTRATION

Adults and children 12 years of age and older: Four tablets every thirty minutes for six doses followed by four tablets every 4-6 hours as needed.

Children 2 years to 12 years of age: Four tablets every thirty minutes for six doses followed by two tablets every 4-6 hours as needed.

Children under 2 years of age: Consult doctor prior to use.

Keep out of reach of children.